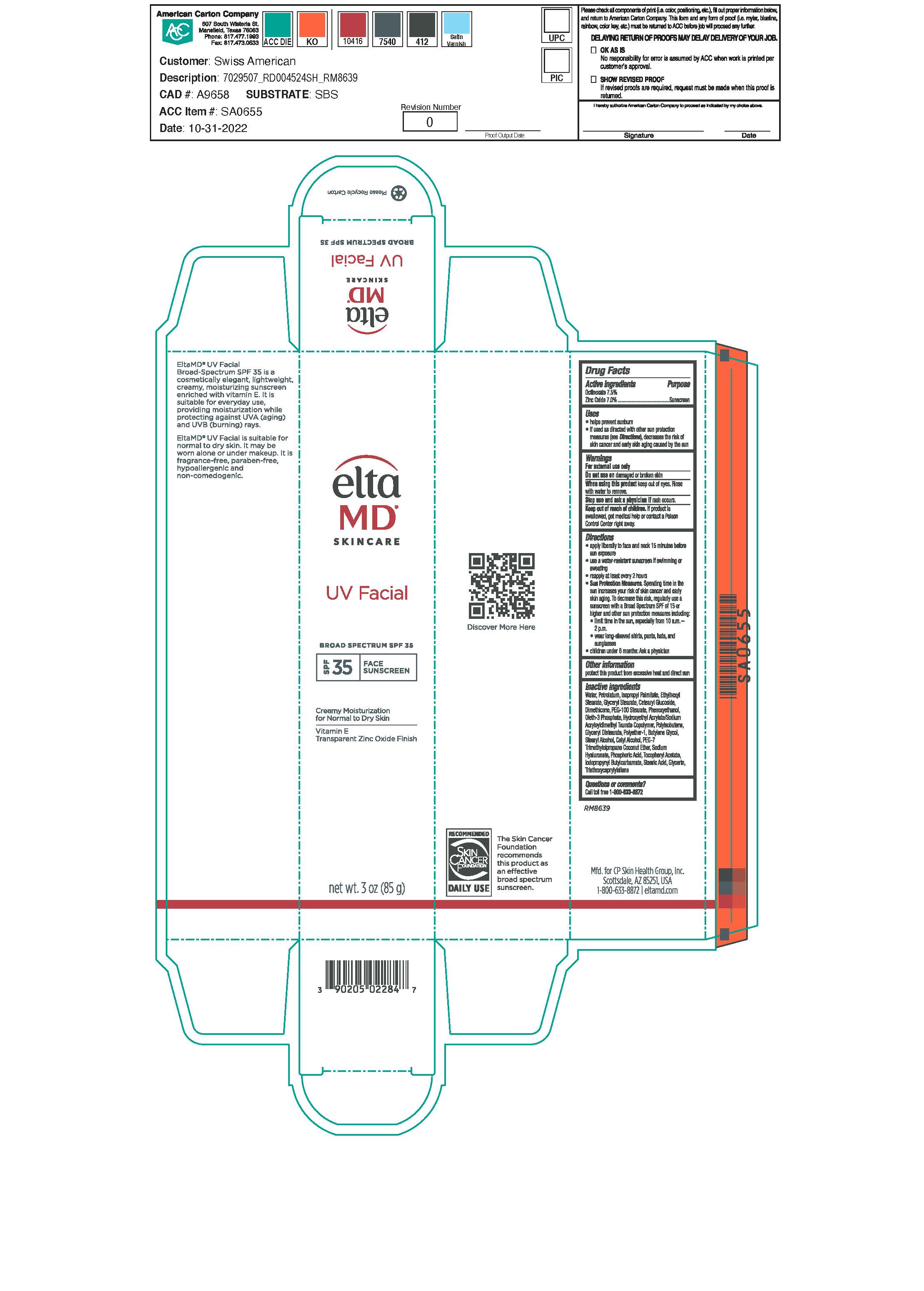 DRUG LABEL: EltaMD UV Facial SPF30 Plus
NDC: 72043-2283 | Form: LOTION
Manufacturer: CP Skin Health Group, Inc.
Category: otc | Type: HUMAN OTC DRUG LABEL
Date: 20231130

ACTIVE INGREDIENTS: ZINC OXIDE 70 g/1000 g; OCTINOXATE 75 g/1000 g
INACTIVE INGREDIENTS: WATER; PHENOXYETHANOL; CETEARYL GLUCOSIDE; PETROLATUM; DIMETHICONE; ISOPROPYL PALMITATE; OCTYL STEARATE; OLETH-3 PHOSPHATE; TRIETHOXYCAPRYLYLSILANE; GLYCERYL STEARATE SE; PEG-100 STEARATE; CITRIC ACID MONOHYDRATE; .ALPHA.-TOCOPHEROL ACETATE, DL-; HYALURONATE SODIUM; HYDROXYETHYL ACRYLATE/SODIUM ACRYLOYLDIMETHYL TAURATE COPOLYMER (100000 MPA.S AT 1.5%); BUTYLENE GLYCOL; IODOPROPYNYL BUTYLCARBAMATE

EltaMD UV Facial SPF30+

Warnings

For external use only Do not use on damaged or broken skin When using this product keep out of eyes. Rinse with warm water to remove Stop use and ask a physician if rash occurs If product is swallowed, get medical help or contact a Poison Control Center right away

Active ingredients

Octinoxate 7.5% Sunscreen

Zinc Oxide 7.0% Sunscreen

Uses

Helps prevent sunburn If used as directed with other sun protection measures (see Directions), decreases the risk of skin cancer and early skin aging caused by the sun.

Uses

Helps prevent sunburn If used as directed with other sun protection measures (see Directions), decreases the risk of skin cancer and early skin aging caused by the sun.

Directions

apply liberally 15 minutes before sun exposure. use a water-resistant sunscreen if swimming or sweating. reapply at least every 2 hours. Sun Protection Measures: Spending time in the sun increases your risk of skin cancer and early skin aging. To decrease this risk, regularly use a sunscreen with a broad-spectrum SPF of 15 or higher another sun protection measures including: limit time in the sun, especially from 10 am - 2 pm wear long-sleeve shirts, pants, hats and sunglasses Children under 6 months: Ask a physician

Inactive Ingredients

purified water, petrolatum, isopropyl palmitate, octyl stearate, glyceryl stearate, cetearyl glucoside, dimethicone, PEG-100 stearate, hydroxyethyl acrylate/sodium acryloyldimethyl tautrate copolymer, polyisobutene, PEG-7 trimethylolpropane coconut ether, sodium hyaluronate, tocopheryl acetate, ployether-1, citric acid, oleth-3 phosphate, phenoxyethanol, butylene glycol, iodopropynyl butylcarbamate, triethoxycaprylylsilane

KEEP OUT OF REACH OF CHILDREN